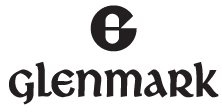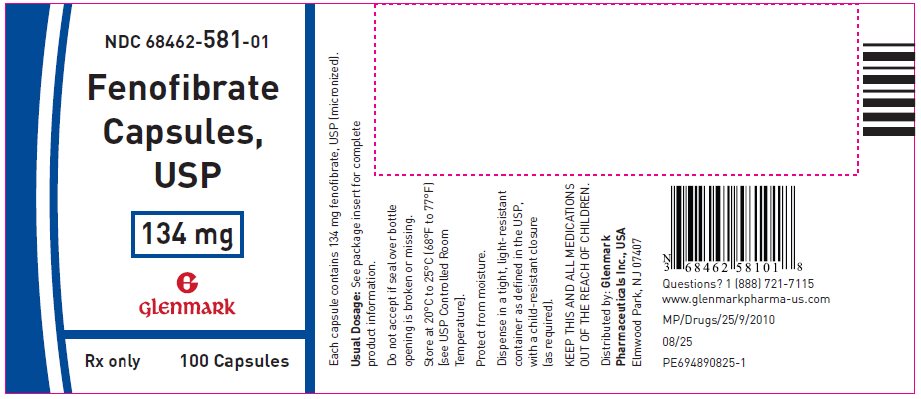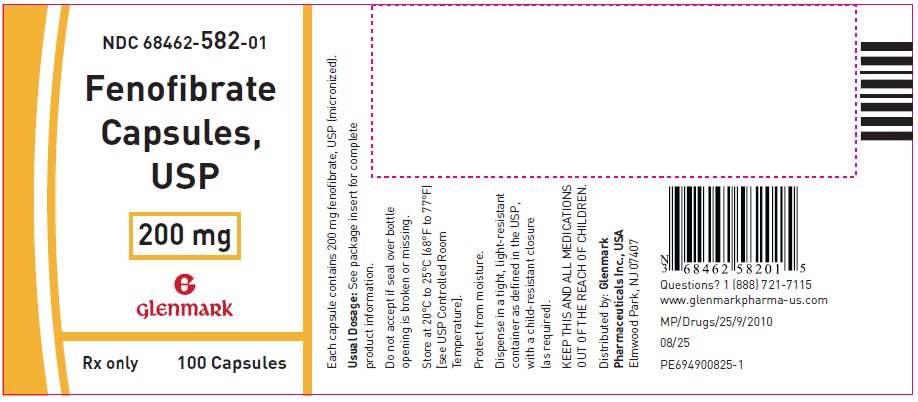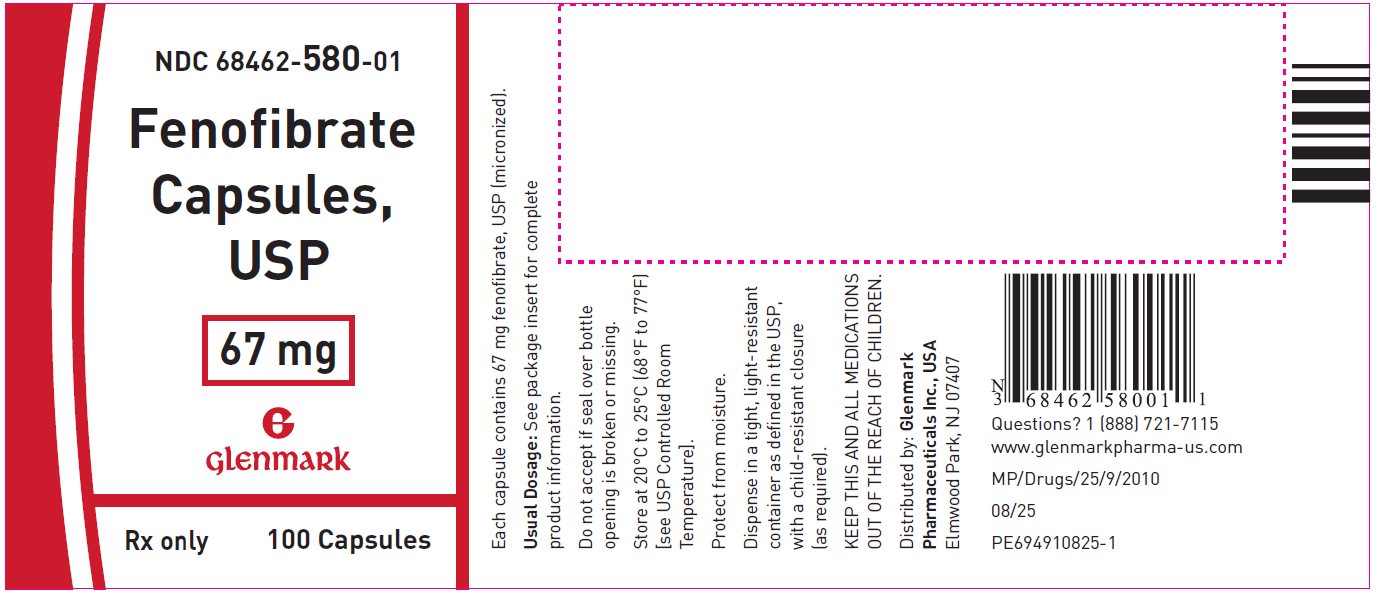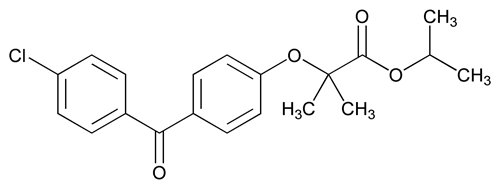 DRUG LABEL: fenofibrate
NDC: 68462-580 | Form: CAPSULE
Manufacturer: Glenmark Pharmaceuticals Inc., USA
Category: prescription | Type: HUMAN PRESCRIPTION DRUG LABEL
Date: 20260131

ACTIVE INGREDIENTS: FENOFIBRATE 67 mg/1 1
INACTIVE INGREDIENTS: SILICON DIOXIDE; CROSPOVIDONE (35 .MU.M); LACTOSE MONOHYDRATE; MAGNESIUM STEARATE; POVIDONE K30; STARCH, CORN; SODIUM LAURYL SULFATE; TALC; D&C RED NO. 28; FD&C BLUE NO. 1; FD&C RED NO. 40; TITANIUM DIOXIDE; GELATIN, UNSPECIFIED; FERROSOFERRIC OXIDE; POTASSIUM HYDROXIDE; SHELLAC

FENOFIBRATE CAPSULES, USP
Rx only

DESCRIPTION

Fenofibrate, USP (micronized), is a lipid regulating agent available as capsules for oral administration. Each capsule contains 67 mg, 134 mg or 200 mg of micronized fenofibrate, USP. The chemical name for fenofibrate, USP is Isopropyl 2-[p-(p-chlorobenzoyl)phenoxy]-2-methylpropanoate with the following structural formula:

The molecular formula is C20H21Cl O4 and the molecular weight is 360.83 g/mol. Fenofibrate, USP is practically insoluble in water, very soluble in methylene chloride and slightly soluble in alcohol. The melting point is 79°C to 82°C. Fenofibrate, USP is a white or almost white, crystalline powder which is stable under ordinary conditions.

Each 67 mg fenofibrate capsule, USP (micronized) contains the following inactive ingredients: black iron oxide, colloidal silicon dioxide, crospovidone, D&C Red #28, FD&C Blue #1, FD&C Red #40, gelatin, lactose monohydrate, magnesium stearate, potassium hydroxide, povidone, pregelatinized starch, shellac, sodium lauryl sulfate, talc and titanium dioxide.

Each 134 mg fenofibrate capsule, USP (micronized) contains the following inactive ingredients: black iron oxide, colloidal silicon dioxide, crospovidone, D&C Red #28, FD&C Blue #1, gelatin, lactose monohydrate, magnesium stearate, potassium hydroxide, povidone, pregelatinized starch, shellac, sodium lauryl sulfate, talc and titanium dioxide.

Each 200 mg fenofibrate capsule, USP (micronized) contains the following inactive ingredients: black iron oxide, colloidal silicon dioxide, crospovidone, D&C Red #28, FD&C Red #40, gelatin, iron oxide yellow, lactose monohydrate, magnesium stearate, potassium hydroxide, povidone, pregelatinized starch, shellac, sodium lauryl sulfate, talc and titanium dioxide.

FDA approved dissolution test specifications differ from USP.

CLINICAL PHARMACOLOGY

A variety of clinical studies have demonstrated that elevated levels of total cholesterol (total-C), low density lipoprotein cholesterol (LDL-C), and apolipoprotein B (apo B), an LDL membrane complex, are associated with human atherosclerosis. Similarly, decreased levels of high density lipoprotein cholesterol (HDL-C) and its transport complex, apolipoprotein A (apo AI and apo AII) are associated with the development of atherosclerosis. Epidemiologic investigations have established that cardiovascular morbidity and mortality vary directly with the level of total-C, LDL-C, and triglycerides, and inversely with the level of HDL-C. The independent effect of raising HDL-C or lowering triglycerides (TG) on the risk of cardiovascular morbidity and mortality has not been determined.

Fenofibric acid, the active metabolite of fenofibrate, produces reductions in total cholesterol, LDL cholesterol, apolipoprotein B, total triglycerides and triglyceride rich lipoprotein (VLDL) in treated patients. In addition, treatment with fenofibrate results in increases in high density lipoprotein (HDL) and apoproteins apo AI and apo AII.

The effects of fenofibric acid seen in clinical practice have been explained in vivo in transgenic mice and in vitro in human hepatocyte cultures by the activation of peroxisome proliferator activated receptor α (PPARα). Through this mechanism, fenofibrate increases lipolysis and elimination of triglyceride-rich particles from plasma by activating lipoprotein lipase and reducing production of apoprotein C-III (an inhibitor of lipoprotein lipase activity). The resulting fall in triglycerides produces an alteration in the size and composition of LDL from small, dense particles (which are thought to be atherogenic due to their susceptibility to oxidation), to large buoyant particles. These larger particles have a greater affinity for cholesterol receptors and are catabolized rapidly. Activation of PPARα also induces an increase in the synthesis of apoproteins A-I, A-II and HDL-cholesterol.

Fenofibrate also reduces serum uric acid levels in hyperuricemic and normal individuals by increasing the urinary excretion of uric acid.

Pharmacokinetics/Metabolism

Clinical experience has been obtained with two different formulations of fenofibrate: a “micronized” and “non-micronized” formulation, which have been demonstrated to be bioequivalent. Comparisons of blood levels following oral administration of both formulations in healthy volunteers demonstrate that a single capsule containing 67 mg of the “micronized” formulation is bioequivalent to 100 mg of the “non-micronized” formulation. Three capsules containing 67 mg fenofibrate are bioequivalent to a single 200 mg fenofibrate capsule.

Absorption

The absolute bioavailability of fenofibrate cannot be determined as the compound is virtually insoluble in aqueous media suitable for injection. However, fenofibrate is well absorbed from the gastrointestinal tract. Following oral administration in healthy volunteers, approximately 60% of a single dose of radiolabelled fenofibrate appeared in urine, primarily as fenofibric acid and its glucuronate conjugate, and 25% was excreted in the feces. Peak plasma levels of fenofibric acid occur within 6 to 8 hours after administration.

The absorption of fenofibrate is increased when administered with food. With micronized fenofibrate, the absorption is increased by approximately 35% under fed as compared to fasting conditions.

Distribution

In healthy volunteers, steady-state plasma levels of fenofibric acid were shown to be achieved within 5 days of dosing with single oral doses equivalent to 67 mg fenofibrate and did not demonstrate accumulation across time following multiple dose administration. Serum protein binding was approximately 99% in normal and hyperlipidemic subjects.

Metabolism

Following oral administration, fenofibrate is rapidly hydrolyzed by esterases to the active metabolite, fenofibric acid; no unchanged fenofibrate is detected in plasma.

Fenofibric acid is primarily conjugated with glucuronic acid and then excreted in urine. A small amount of fenofibric acid is reduced at the carbonyl moiety to a benzhydrol metabolite which is, in turn, conjugated with glucuronic acid and excreted in urine.

In vivo metabolism data indicate that neither fenofibrate nor fenofibric acid undergo oxidative metabolism (e.g., cytochrome P450) to a significant extent.

Excretion

After absorption, fenofibrate is mainly excreted in the urine in the form of metabolites, primarily fenofibric acid and fenofibric acid glucuronide. After administration of radiolabelled fenofibrate, approximately 60% of the dose appeared in the urine and 25% was excreted in the feces.

Fenofibric acid is eliminated with a half-life of 20 hours, allowing once daily administration in a clinical setting.

Special Populations

Geriatrics

In elderly volunteers 77 to 87 years of age, the oral clearance of fenofibric acid following a single oral dose of fenofibrate was 1.2 L/h, which compares to 1.1 L/h in young adults. This indicates that a similar dosage regimen can be used in the elderly, without increasing accumulation of the drug or metabolites.

Pediatrics

Fenofibrate has not been investigated in adequate and well-controlled trials in pediatric patients.

Gender

No pharmacokinetic difference between males and females has been observed for fenofibrate.

Race

The influence of race on the pharmacokinetics of fenofibrate has not been studied, however fenofibrate is not metabolized by enzymes known for exhibiting inter-ethnic variability. Therefore, inter-ethnic pharmacokinetic differences are very unlikely.

Renal Insufficiency

The pharmacokinetics of fenofibric acid was examined in patients with mild, moderate and severe renal impairment. Patients with severe renal impairment (creatinine clearance [CrCl] ≤ 30 mL/min) showed 2.7-fold increase in exposure for fenofibric acid and increased accumulation of fenofibric acid during chronic dosing compared to that of healthy subjects. Patients with mild to moderate renal impairment (CrCl 30 to 80 mL/min) had similar exposure but an increase in the half-life for fenofibric acid compared to that of healthy subjects. Based on these findings, the use of fenofibrate should be avoided in patients who have severe renal impairment and dose reduction is required in patients having mild to moderate renal impairment.

Hepatic Insufficiency

No pharmacokinetic studies have been conducted in patients having hepatic insufficiency.

Drug-Drug Interactions

In vitro studies using human liver microsomes indicate that fenofibrate and fenofibric acid are not inhibitors of cytochrome (CYP) P450 isoforms CYP3A4, CYP2D6, CYP2E1, or CYP1A2. They are weak inhibitors of CYP2C19 and CYP2A6, and mild-to-moderate inhibitors of CYP2C9 at therapeutic concentrations.

Potentiation of coumarin-type anti-coagulants has been observed with prolongation of the prothrombin time/INR.

Bile acid sequestrants have been shown to bind other drugs given concurrently. Therefore, fenofibrate should be taken at least 1 hour before or 4 to 6 hours after a bile acid binding resin to avoid impeding its absorption (see WARNINGS and PRECAUTIONS).

Concomitant administration of a single dose of fenofibrate (administered as 3 X 67 mg fenofibrate micronized capsules) with a single dose of pravastatin (40 mg) in 23 healthy subjects increased the mean Cmax and mean AUC for pravastatin by 13%. The Cmax and AUC of fenofibrate decreased by 2% and 1%, respectively, after concomitant administration of fenofibrate and pravastatin. The mean Cmax and AUC for 3α-hydroxy-iso-pravastatin increased by 29% and 26%, respectively.

Concomitant administration of a single dose of fenofibrate (equivalent to 145 mg fenofibrate) and a single dose of fluvastatin (40 mg) resulted in a small increase (approximately 15% to 16%) in exposure to (+)3R,5S-fluvastatin, the active enantiomer of fluvastatin.

A single dose of either pravastatin or fluvastatin had no clinically important effect on the pharmacokinetics of fenofibric acid.

Concomitant administration of fenofibrate (equivalent to fenofibrate 200 mg) with atorvastatin (20 mg) once daily for 10 days resulted in approximately 17% decrease (range from 67% decrease to 44% increase) in atorvastatin AUC values in 22 healthy males. The atorvastatin Cmax values were not significantly affected by fenofibrate. The pharmacokinetics of fenofibric acid were not significantly affected by atorvastatin.

Concomitant administration of fenofibrate (equivalent to fenofibrate 200 mg) once daily for 10 days with glimepiride (1 mg tablet) single dose simultaneously with the last dose of fenofibrate resulted in a 35% increase in mean AUC of glimepiride in healthy subjects. Glimepiride Cmax was not significantly affected by fenofibrate coadministration. There was no statistically significant effect of multiple doses of fenofibrate on glucose nadir or AUC with the baseline glucose concentration as the covariate after glimepiride administration in healthy volunteers. However, glucose concentrations at 24 hours remained statistically significantly lower after pretreatment with fenofibrate than with glimepiride alone. Glimepiride had no significant effect on the pharmacokinetics of fenofibric acid.

Concomitant administration of fenofibrate (54 mg) and metformin (850 mg) three times a day for 10 days resulted in no significant changes in the pharmacokinetics of fenofibric acid and metformin when compared with the two drugs administered alone in healthy subjects.

Concomitant administration of fenofibrate (equivalent to fenofibrate 200 mg) once daily for 14 days with rosiglitazone tablet (rosiglitazone maleate) (8 mg) once daily for 5 days, Day 10 through Day 14, resulted in no significant changes in the pharmacokinetics of fenofibric acid and rosiglitazone when compared with the two drugs administered alone in healthy subjects.

Clinical Trials

Hypercholesterolemia (Heterozygous Familial and Nonfamilial) and Mixed Dyslipidemia (Fredrickson Types IIa and IIb)

The effects of fenofibrate at a dose equivalent to 200 mg fenofibrate per day were assessed from four randomized, placebo-controlled, double-blind, parallel-group studies including patients with the following mean baseline lipid values: total-C 306.9 mg/dL; LDL-C 213.8 mg/dL; HDL-C 52.3 mg/dL; and triglycerides 191 mg/dL. Fenofibrate therapy lowered LDL-C, Total-C, and the LDL-C/HDL-C ratio. Fenofibrate therapy also lowered triglycerides and raised HDL-C (see Table 1).

Table 1: Mean Percent Change in Lipid Parameters at End of Treatmenta
Treatment Group | Total-C | LDL-C | HDL-C | TG
Pooled Cohort
Mean baseline lipid values (n=646) | 306.9 mg/dL | 213.8 mg/dL | 52.3 mg/dL | 191 mg/dL
All FEN (n=361) | -18.7%b | -20.6%b | +11%b | -28.9%b
Placebo (n=285) | -0.4% | -2.2% | +0.7% | +7.7%
Baseline LDL-C > 160 mg/dL and TG < 150 mg/dL (Type IIa)
Mean baseline lipid values (n=334) | 307.7 mg/dL | 227.7 mg/dL | 58.1 mg/dL | 101.7 mg/dL
All FEN (n=193) | -22.4%b | -31.4%b | +9.8% | -23.5%b
Placebo (n=141) | +0.2% | -2.2% | +2.6% | +11.7%
Baseline LDL-C > 160 mg/dL and; TG ≥ 150 mg/dL (Type IIb)
Mean baseline lipid values (n=242) | 312.8 mg/dL | 219.8 mg/dL | 46.7 mg/dL | 231.9 mg/dL
All FEN (n=126) | -16.8%b | -20.1%b | +14.6%b | -35.9%b
Placebo (n=116) | -3% | -6.6% | +2.3% | +0.9%
a Duration of study treatment was 3 to 6 months
b p = <0.05 vs. Placebo
In a subset of the subjects, measurements of apo B were conducted. Fenofibrate treatment significantly reduced apo B from baseline to endpoint as compared with placebo (-25.1% vs. 2.4%, p<0.0001, n=213 and 143 respectively).

Hypertriglyceridemia (Fredrickson Type IV and V)

The effects of fenofibrate on serum triglycerides were studied in two randomized, double-blind, placebo-controlled clinical trials^1 of 147 hypertriglyceridemia patients (Fredrickson Types IV and V). Patients were treated for eight weeks under protocols that differed only in that one entered patients with baseline triglyceride (TG) levels of 500 to 1500 mg/dL, and the other TG levels of 350 to 500 mg/dL. In patients with hypertriglyceridemia and normal cholesterolemia with or without hyperchylomicronemia (Type IV/V hyperlipidemia), treatment with fenofibrate at dosages equivalent to 200 mg fenofibrate per day decreased primarily very low density lipoprotein (VLDL) triglycerides and VLDL cholesterol. Treatment of patients with Type IV hyperlipoproteinemia and elevated triglycerides often results in an increase of low density lipoprotein (LDL) cholesterol (see Table 2).

Table 2: Effects of Fenofibrate Capsules in Patients with Fredrickson Type IV/V Hyperlipidemia
Study 1 | Placebo |  |  |  | Fenofibrate Capsules
Baseline TG levels 350 to 499 mg/dL | N | Baseline (Mean) | Endpoint (Mean) | % Change (Mean) | N | Baseline (Mean) | Endpoint (Mean) | % Change (Mean)
Triglycerides | 28 | 449 | 450 | -0.5 | 27 | 432 | 223 | -46.2a
VLDL Triglycerides | 19 | 367 | 350 | 2.7 | 19 | 350 | 178 | -44.1a
Total Cholesterol | 28 | 255 | 261 | 2.8 | 27 | 252 | 227 | -9.1a
HDL Cholesterol | 28 | 35 | 36 | 4 | 27 | 34 | 40 | 19.6a
LDL Cholesterol | 28 | 120 | 129 | 12 | 27 | 128 | 137 | 14.5
VLDL Cholesterol | 27 | 99 | 99 | 5.8 | 27 | 92 | 46 | -44.7a
Study 2 | Placebo |  |  |  | Fenofibrate Capsules
Baseline TG levels 500 to 1500 mg/dL | N | Baseline (Mean) | Endpoint (Mean) | % Change (Mean) | N | Baseline (Mean) | Endpoint (Mean) | % Change (Mean)
Triglycerides | 44 | 710 | 750 | 7.2 | 48 | 726 | 308 | -54.5a
VLDL Triglycerides | 29 | 537 | 571 | 18.7 | 33 | 543 | 205 | -50.6a
Total Cholesterol | 44 | 272 | 271 | 0.4 | 48 | 261 | 223 | -13.8a
HDL Cholesterol | 44 | 27 | 28 | 5 | 48 | 30 | 36 | 22.9a
LDL Cholesterol | 42 | 100 | 90 | -4.2 | 45 | 103 | 131 | 45a
VLDL Cholesterol | 42 | 137 | 142 | 11 | 45 | 126 | 54 | -49.4a
a p<0.05 vs. Placebo

The effect of fenofibrate on cardiovascular morbidity and mortality has not been determined.

INDICATIONS AND USAGE

Treatment of Hypercholesterolemia

Fenofibrate capsules are indicated as adjunctive therapy to diet for the reduction of LDL-C, Total-C, Triglycerides and Apo B in adult patients with primary hypercholesterolemia or mixed dyslipidemia (Fredrickson Types IIa and IIb). Lipid-altering agents should be used in addition to a diet restricted in saturated fat and cholesterol when response to diet and non-pharmacological interventions alone has been inadequate (see National Cholesterol Education Program [NCEP] Treatment Guidelines, below).

Treatment of Hypertriglyceridemia

Fenofibrate capsules are also indicated as adjunctive therapy to diet for treatment of adult patients with hypertriglyceridemia (Fredrickson Types IV and V hyperlipidemia).

Improving glycemic control in diabetic patients showing fasting chylomicronemia will usually reduce fasting triglycerides and eliminate chylomicronemia thereby obviating the need for pharmacologic intervention.

Markedly elevated levels of serum triglycerides (e.g. > 2,000 mg/dL) may increase the risk of developing pancreatitis. The effect of fenofibrate therapy on reducing this risk has not been adequately studied.

Drug therapy is not indicated for patients with Type I hyperlipoproteinemia, who have elevations of chylomicrons and plasma triglycerides, but who have normal levels of very low density lipoprotein (VLDL). Inspection of plasma refrigerated for 14 hours is helpful in distinguishing Types I, IV and V hyperlipoproteinemia^2.

The initial treatment for dyslipidemia is dietary therapy specific for the type of lipoprotein abnormality. Excess body weight and excess alcoholic intake may be important factors in hypertriglyceridemia and should be addressed prior to any drug therapy. Physical exercise can be an important ancillary measure. Diseases contributory to hyperlipidemia, such as hypothyroidism or diabetes mellitus should be looked for and adequately treated. Estrogen therapy, like thiazide diuretics and beta-blockers, is sometimes associated with massive rises in plasma triglycerides, especially in subjects with familial hypertriglyceridemia. In such cases, discontinuation of the specific etiologic agent may obviate the need for specific drug therapy of hypertriglyceridemia.

The use of drugs should be considered only when reasonable attempts have been made to obtain satisfactory results with non-drug methods. If the decision is made to use drugs, the patient should be instructed that this does not reduce the importance of adhering to diet (see WARNINGSandPRECAUTIONS).

Fredrickson Classification of Hyperlipoproteinemias

 |  | Lipid Elevation
Type | Lipoprotein Elevated | Major | Minor
I (rare) | Chylomicrons | TG | ↑↔C
IIa | LDL | C | -
IIb | LDL, VLDL | C | TG
III (rare) | IDL | C, TG | -
IV | VLDL | TG | ↑↔C
V (rare) | Chylomicrons, VLDL | TG | ↑↔

C = cholesterol
TG = triglycerides
LDL = low density lipoprotein
VLDL = very low density lipoprotein
IDL = intermediate density lipoprotein
The NCEP Treatment Guidelines

 |  | LDL-Cholesterol mg/dL (mmol/L)
Definite Atherosclerotic Disease^1 | Two or More Other Risk Factors^2 | Initiation Level | Goal
No | No | ≥ 190 (≥ 4.9) | < 160 (< 4.1)
No | Yes | ≥ 160 (≥ 4.1) | < 130 (< 3.4)
Yes | Yes or No | ≥ 130^3 (≥ 3.4) | < 100 (< 2.6)

^1Coronary heart disease or peripheral vascular disease (including symptomatic carotid artery disease).

^2Other risk factors for coronary heart disease (CHD) include: age (males: ≥ 45 years; females: ≥ 55 years or premature menopause without estrogen replacement therapy); family history of premature CHD; current cigarette smoking; hypertension; confirmed HDL-C < 35 mg/dL (< 0.91 mmol/L); and diabetes mellitus. Subtract 1 risk factor if HDL-C is ≥ 60 mg/dL (≥ 1.6 mmol/L).

^3In CHD patients with LDL-C levels 100 to 129 mg/dL, the physician should exercise clinical judgment in deciding whether to initiate drug treatment.

CONTRAINDICATIONS

Fenofibrate capsules are contraindicated in patients who exhibit hypersensitivity to fenofibrate.

Fenofibrate capsules are contraindicated in patients with hepatic or severe renal dysfunction, including primary biliary cirrhosis, and patients with unexplained persistent liver function abnormality.

Fenofibrate capsules are contraindicated in patients with preexisting gallbladder disease (see WARNINGS).

WARNINGS

Hepatotoxicity

Serious drug-induced liver injury (DILI), including liver transplantation and death, have been reported postmarketing with fenofibrate. DILI has been reported within the first few weeks of treatment or after several months of therapy and in some cases has reversed with discontinuation of fenofibrate treatment. Patients with DILI have experienced signs and symptoms including dark urine, abnormal stool, jaundice, malaise, abdominal pain, myalgia, weight loss, pruritus, and nausea. Many patients had concurrent elevations of total bilirubin, serum alanine transaminase (ALT), and aspartate transaminase (AST). DILI has been characterized as hepatocellular, chronic active, and cholestatic hepatitis, and cirrhosis has occurred in association with chronic active hepatitis

In clinical trials, fenofibrate at doses equivalent to 134 mg to 200 mg fenofibrate daily has been associated with increases in serum AST or ALT. The incidence of increases in transaminases may be dose-related.

Fenofibrate is contraindicated in patients with active liver disease, including those with primary biliary cirrhosis and unexplained persistent liver function abnormalities [see CONTRAINDICATIONS]. Monitor patient’s liver function, including serum ALT, AST, and total bilirubin, at baseline and periodically for the duration of therapy with fenofibrate. Discontinue fenofibrate if signs or symptoms of liver injury develop or if elevated enzyme levels persist (ALT or AST > 3 times the upper limit of normal, or if accompanied by elevation of bilirubin). Do not restart fenofibrate in these patients if there is no alternative explanation for the liver injury.

Cholelithiasis

Fenofibrate, like clofibrate and gemfibrozil, may increase cholesterol excretion into the bile, leading to cholelithiasis. If cholelithiasis is suspected, gallbladder studies are indicated. Fenofibrate therapy should be discontinued if gallstones are found.

Concomitant Oral Anticoagulants

Caution should be exercised when anticoagulants are given in conjunction with fenofibrate because of the potentiation of coumarin-type anticoagulants in prolonging the prothrombin time/INR. The dosage of the anticoagulant should be reduced to maintain the prothrombin time/INR at the desired level to prevent bleeding complications. Frequent prothrombin time/INR determinations are advisable until it has been definitely determined that the prothrombin time/INR has stabilized.

Concomitant HMG-CoA Reductase Inhibitors

The combined use of fenofibrate and HMG-CoA reductase inhibitors should be avoided unless the benefit of further alterations in lipid levels is likely to outweigh the increased risk of this drug combination.

Concomitant administration of fenofibrate (equivalent to fenofibrate 200 mg) and pravastatin (40 mg) once daily for 10 days increased the mean Cmax and AUC values for pravastatin by 36% (range from 69% decrease to 321% increase) and 28% (range from 54% decrease to 128% increase), respectively, and for 3α-hydroxy-iso-pravastatin by 55% (range from 32% decrease to 314% increase) and 39% (range from 24% decrease to 261% increase), respectively (see also CLINICAL PHARMACOLOGY, Drug-Drug Interactions).

The combined use of fibric acid derivatives and HMG-CoA reductase inhibitors has been associated, in the absences of a marked pharmacokinetic interaction, in numerous case reports, with rhabdomyolysis, markedly elevated creatine kinase (CK) levels and myoglobinuria, leading in a high proportion of cases to acute renal failure.

The use of fibrates alone, including fenofibrate capsules may occasionally be associated with myositis, myopathy, or rhabdomyolysis. Patients receiving fenofibrate and complaining of muscle pain, tenderness, or weakness should have prompt medical evaluation for myopathy, including serum creatine kinase level determination. If myopathy/myositis is suspected or diagnosed, fenofibrate therapy should be stopped.

Mortality

The effect of fenofibrate on coronary heart disease morbidity and mortality and non-cardiovascular mortality has not been established.

Other Considerations

The Fenofibrate Intervention and Event Lowering in Diabetes (FIELD) study was a 5-year randomized, placebo-controlled study of 9,795 patients with type 2 diabetes mellitus treated with fenofibrate.

Fenofibrate demonstrated a non-significant 11% relative reduction in the primary outcome of coronary heart disease events (hazard ratio [HR] 0.89, 95% CI 0.75 to 1.05, p=0.16) and a significant 11% reduction in the secondary outcome of total cardiovascular disease events (HR 0.89 [0.80 to 0.99], p=0.04). There was a non-significant 11% (HR 1.11 [0.95, 1.29], p=0.18) and 19% (HR 1.19 [0.9, 1.57], p=0.22) increase in total and coronary heart disease mortality, respectively, with fenofibrate as compared to placebo.

In the Coronary Drug Project, a large study of post myocardial infarction of patients treated for 5 years with clofibrate, there was no difference in mortality seen between the clofibrate group and the placebo group. There was however, a difference in the rate of cholelithiasis and cholecystitis requiring surgery between the two groups (3% vs. 1.8%).

Because of chemical, pharmacological, and clinical similarities between fenofibrate, clofibrate, and gemfibrozil, the adverse findings in 4 large randomized, placebo-controlled clinical studies with these other fibrate drugs may also apply to fenofibrate.

In a study conducted by the World Health Organization (WHO), 5000 subjects without known coronary artery disease were treated with placebo or clofibrate for 5 years and followed for an additional one year. There was a statistically significant, higher age-adjusted all-cause mortality in the clofibrate group compared with the placebo group (5.7% vs. 3.96%, p=<0.01). Excess mortality was due to a 33% increase in non-cardiovascular causes, including malignancy, post-cholecystectomy complications, and pancreatitis. This appeared to confirm the higher risk of gallbladder disease seen in clofibrate-treated patients studied in the Coronary Drug Project.

The Helsinki Heart Study was a large (n=4081) study of middle-aged men without a history of coronary artery disease. Subjects received either placebo or gemfibrozil for 5 years, with a 3.5 year open extension afterward. Total mortality was numerically higher in the gemfibrozil randomization group but did not achieve statistical significance (p=0.19, 95% confidence interval for relative risk G:P=0.91 to 1.64). Although cancer deaths trended higher in the gemfibrozil group (p=0.11), cancers (excluding basal cell carcinoma) were diagnosed with equal frequency in both study groups. Due to the limited size of the study, the relative risk of death from any cause was not shown to be different than that seen in the 9 year follow-up data from World Health Organization study (RR=1.29). Similarly, the numerical excess of gallbladder surgeries in the gemfibrozil group did not differ statistically from that observed in the WHO study.

A secondary prevention component of the Helsinki Heart Study enrolled middle-aged men excluded from the primary prevention study because of known or suspected coronary heart disease. Subjects received gemfibrozil or placebo for 5 years. Although cardiac deaths trended higher in the gemfibrozil group, this was not statistically significant (hazard ratio 2.2, 95% confidence interval: 0.94 to 5.05). The rate of gallbladder surgery was not statistically significant between study groups, but did trend higher in the gemfibrozil group, (1.9% vs. 0.3%, p=0.07). There was a statistically significant difference in the number of appendectomies in the gemfibrozil group (6/311 vs. 0/317, p=0.029).

PRECAUTIONS

Initial Therapy

Laboratory studies should be done to ascertain that the lipid levels are consistently abnormal before instituting fenofibrate therapy. Every attempt should be made to control serum lipids with appropriate diet, exercise, weight loss in obese patients, and control of any medical problems such as diabetes mellitus and hypothyroidism that are contributing to the lipid abnormalities. Medications known to exacerbate hypertriglyceridemia (beta-blockers, thiazides, estrogens) should be discontinued or changed if possible prior to consideration of triglyceride-lowering drug therapy.

Continued Therapy

Periodic determination of serum lipids should be obtained during initial therapy in order to establish the lowest effective dose of fenofibrate capsules. Therapy should be withdrawn in patients who do not have an adequate response after two months of treatment with the maximum recommended dose of 200 mg per day.

Pancreatitis

Pancreatitis has been reported in patients taking fenofibrate, gemfibrozil, and clofibrate. This occurrence may represent a failure of efficacy in patients with severe hypertriglyceridemia, a direct drug effect, or a secondary phenomenon mediated through biliary tract stone or sludge formation with obstruction of the common bile duct.

Hypersensitivity Reactions

Acute Hypersensitivity:

Anaphylaxis and angioedema have been reported postmarketing with fenofibrate. In some cases, reactions were life-threatening and required emergency treatment. If a patient develops signs or symptoms of an acute hypersensitivity reaction, advise them to seek immediate medical attention and discontinue fenofibrate.

Delayed Hypersensitivity:

Severe cutaneous adverse drug reactions (SCAR), including Stevens-Johnson Syndrome, Toxic Epidermal Necrolysis, and Drug Reaction with Eosinophilia and Systemic Symptoms (DRESS), have been reported postmarketing, occurring days to weeks after initiation of fenofibrate. The cases of DRESS were associated with cutaneous reactions (such as rash or exfoliative dermatitis) and a combination of eosinophilia, fever, systemic organ involvement (renal, hepatic, or respiratory). Discontinue fenofibrate and treat patients appropriately if SCAR is suspected.

Hematologic Changes

Mild to moderate hemoglobin, hematocrit and white blood cell decreases have been observed in patients following initiation of fenofibrate therapy. However, these levels stabilize during long-term administration. Extremely rare spontaneous reports of thrombocytopenia and agranulocytosis have been received during post-marketing surveillance outside of the U.S. Periodic blood counts are recommended during the first 12 months of fenofibrate administration.

Myopathy and Rhabdomyolysis

The use of fibrates alone, including fenofibrate, may occasionally be associated with myopathy. Treatment with drugs of the fibrate class has been associated on rare occasions with rhabdomyolysis, usually in patients with impaired renal function. Myopathy should be considered in any patient with diffuse myalgias, muscle tenderness or weakness, and/or marked elevations of creatine phosphokinase levels.

Patients should be advised to report promptly unexplained muscle pain, tenderness or weakness, particularly if accompanied by malaise or fever. CPK levels should be assessed in patients reporting these symptoms and fenofibrate therapy should be discontinued if markedly elevated CPK levels occur or myopathy is diagnosed.

Venothromboembolic Disease

In the FIELD trial, pulmonary embolus (PE) and deep vein thrombosis (DVT) were observed at higher rates in the fenofibrate- than the placebo-treated group. Of 9,795 patients enrolled in FIELD, there were 4,900 in the placebo group and 4,895 in the fenofibrate group. For DVT, there were 48 events (1%) in the placebo group and 67 (1%) in the fenofibrate group (p = 0.074); and for PE, there were 32 (0.7%) events in the placebo group and 53 (1%) in the fenofibrate group (p = 0.022).

In the Coronary Drug Project, a higher proportion of the clofibrate group experienced definite or suspected fatal or nonfatal pulmonary embolism or thrombophlebitis than the placebo group (5.2% vs. 3.3% at five years; p < 0.01).

Serum Creatinine

Elevations in serum creatinine have been reported in patients on fenofibrate. These elevations tend to return to baseline following discontinuation of fenofibrate. The clinical significance of these observations is unknown.

Drug Interactions

Oral Anticoagulants

CAUTION SHOULD BE EXERCISED WHEN COUMARIN ANTICOAGULANTS ARE GIVEN IN CONJUNCTION WITH FENOFIBRATE. THE DOSAGE OF THE ANTICOAGULANTS SHOULD BE REDUCED TO MAINTAIN THE PROTHROMBIN TIME/INR AT THE DESIRED LEVEL TO PREVENT BLEEDING COMPLICATIONS. FREQUENT PROTHROMBIN TIME/INR DETERMINATIONS ARE ADVISABLE UNTIL IT HAS BEEN DEFINITELY DETERMINED THAT THE PROTHROMBIN TIME/INR HAS STABILIZED.

HMG-CoA Reductase Inhibitors

The combined use of fenofibrate and HMG-CoA reductase inhibitors should be avoided unless the benefit of further alterations in lipid levels is likely to outweigh the increased risk of this drug combination (see WARNINGS).

Resins

Since bile acid sequestrants may bind other drugs given concurrently, patients should take fenofibrate capsules at least one hour before or 4 to 6 hours after a bile acid binding resin to avoid impeding its absorption.

Cyclosporine

Because cyclosporine can produce nephrotoxicity with decreases in creatinine clearance and rises in serum creatinine and because renal excretion is the primary elimination route of fibrate drugs including fenofibrate, there is a risk that an interaction will lead to deterioration. The benefits and risks of using fenofibrate with immunosuppressants and other potentially nephrotoxic agents should be carefully considered and the lowest effective dose employed.

Carcinogenesis, Mutagenesis, Impairment of Fertility

Two dietary carcinogenicity studies have been conducted in rats with fenofibrate. In the first 24-month study, rats were dosed with fenofibrate at 10, 45 and 200 mg/kg/day, approximately 0.3, 1 and 6 times the maximum recommended human dose (MRHD), based on body surface area comparisons (mg/m^2). At a dose of 200 mg/kg/day (at 6 times the MRHD), the incidence of liver carcinomas was significantly increased in both sexes. A statistically significant increase in pancreatic carcinomas was observed in males at 1 and 6 times the MRHD; an increase in pancreatic adenomas and benign testicular interstitial cell tumors was observed at 6 times the MRHD in males. In a second 24-month rat carcinogenicity study in a different strain of rats, doses of 10 and 60 mg/kg/day (0.3 and 2 times the MRHD) produced significant increases in the incidence of pancreatic acinar adenomas in both sexes and increases in testicular interstitial cell tumors in males at 2 times the MRHD.

A 117-week carcinogenicity study was conducted in rats comparing three drugs: fenofibrate 10 and 60 mg/kg/day (0.3 and 2 times the MRHD), clofibrate (400 mg/kg/day; 2 times the human dose) and gemfibrozil (250 mg/kg/day; 2 times the human dose, based on mg/m^2 surface area). Fenofibrate increased pancreatic acinar adenomas in both sexes. Clofibrate increased hepatocellular carcinoma and pancreatic acinar adenomas in males and hepatic neoplastic nodules in females. Gemfibrozil increased hepatic neoplastic nodules in males and females, while all three drugs increased testicular interstitial cell tumors in males.

In a 21-month study in mice, fenofibrate 10, 45 and 200 mg/kg/day (approximately 0.2, 1 and 3 times the MRHD on the basis of mg/m^2 surface area) significantly increased the liver carcinomas in both sexes at 3 times the MRHD. In a second 18-month study at 10, 60 and 200 mg/kg/day, fenofibrate significantly increased the liver carcinomas in male mice and liver adenomas in female mice at 3 times the MRHD.

Electron microscopy studies have demonstrated peroxisomal proliferation following fenofibrate administration to the rat. An adequate study to test for peroxisome proliferation in humans has not been done, but changes in peroxisome morphology and numbers have been observed in humans after treatment with other members of the fibrate class when liver biopsies were compared before and after treatment in the same individual.

Fenofibrate has been demonstrated to be devoid of mutagenic potential in the following tests: Ames, mouse lymphoma, chromosomal aberration and unscheduled DNA synthesis in primary rat hepatocytes.

In fertility studies rats were given oral dietary doses of fenofibrate, males received 61 days prior to mating and females 15 days prior to mating through weaning which resulted in no adverse effect on fertility at doses up to 300 mg/kg/day (~ 10 times the MRHD, based on mg/m^2 surface area comparisons).

Teratogenic Effects

Safety in pregnant women has not been established. There are no adequate and well controlled studies of fenofibrate in pregnant women. Fenofibrate should be used during pregnancy only if the potential benefit justifies the potential risk to the fetus.

In female rats given oral dietary doses of 15, 75 and 300 mg/kg/day of fenofibrate from 15 days prior to mating through weaning, maternal toxicity was observed at 0.3 times the MRHD, based on body surface area comparisons; mg/m^2.

In pregnant rats given oral dietary doses of 14, 127 and 361 mg/kg/day from gestation day 6 to 15 during the period of organogenesis, adverse developmental findings were not observed at 14 mg/kg/day (less than 1 times the MRHD, based on body surface area comparisons; mg/m^2). At higher multiples of human doses evidence of maternal toxicity was observed. In pregnant rabbits given oral gavage doses of 15, 150 and 300 mg/kg/day from gestation day 6 to 18 during the period of organogenesis and allowed to deliver, aborted litters were observed at 150 mg/kg/day (10 times the MRHD, based on body surface area comparisons; mg/m^2). No developmental findings were observed at 15 mg/kg/day (at less than 1 times the MRHD, based on body surface area comparisons; mg/m^2).

In pregnant rats given oral dietary doses of 15, 75 and 300 mg/kg/day from gestation Day 15 through lactation Day 21 (weaning), maternal toxicity was observed at less than 1 times the MRHD, based on body surface area comparisons; mg/m^2.

Nursing Mothers

It is not known whether fenofibrate is excreted into milk. Because many drugs are excreted in human milk and because of the potential for serious adverse reactions in nursing infants from fenofibrate, a decision should be made whether to discontinue nursing or administration of fenofibrate taking into account the importance of the drug to the lactating woman.

Pediatric Use

Safety and efficacy in pediatric patients have not been established.

Geriatric Use

Fenofibric acid is known to be substantially excreted by the kidney, and the risk of adverse reactions to this drug may be greater in patients with impaired renal function. Fenofibric acid exposure is not influenced by age. However, elderly patients have a higher incidence of renal impairment, such that dose selection for the elderly should be made on the basis of renal function (see CLINICAL PHARMACOLOGY, Special Populations, Renal Insufficiency). Elderly patients with normal renal function should require no dose modifications.

ADVERSE REACTIONS

Clinical Studies Experience

Because clinical studies are conducted under widely varying conditions, adverse reaction rates observed in the clinical studies of a drug cannot be directly compared to rates in the clinical studies of another drug and may not reflect the rates observed in practice.

Adverse events reported by 2% or more of patients treated with fenofibrate (and greater than placebo) during the double-blind, placebo-controlled trials, regardless of causality, are listed in Table 3 below. Adverse events led to discontinuation of treatment in 5% of patients treated with fenofibrate and in 3% treated with placebo. Increases in liver function tests were the most frequent events, causing discontinuation of fenofibrate treatment in 1.6% of patients in double-blind trials.

Photosensitivity reactions have occurred days to months after initiation; in some of these cases, patients reported a prior photosensitivity reaction to ketoprofen.

Table 3. Adverse Reactions Reported by 2% or More of Patients Treated with Fenofibrate and Greater than Placebo During the Double-Blind, Placebo-Controlled Trials
BODY SYSTEM; Adverse Reaction | Fenofibratea; (N=439) | PLACEBO; (N=365)
BODY AS A WHOLE
Abdominal Pain | 4.6% | 4.4%
Back Pain | 3.4% | 2.5%
Headache | 3.2% | 2.7%
DIGESTIVE
Abnormal Liver Function Tests | 7.5%b | 1.4%
Nausea | 2.3% | 1.9%
Constipation | 2.1% | 1.4%
METABOLIC AND NUTRITIONAL DISORDERS
Increased ALT | 3% | 1.6%
Increased CPK | 3% | 1.4%
Increased AST | 3.4% b | 0.5%
RESPIRATORY
Respiratory Disorder | 6.2% | 5.5%
Rhinitis | 2.3% | 1.1%
a Dosage equivalent to 145 mg fenofibrate
b Significantly different from Placebo

Increases in Liver Enzymes

In a pooled analysis of 10 placebo-controlled trials, increases to >3 times the upper limit of normal in ALT occurred in 5.3% of patients taking fenofibrate versus 1.1% of patients treated with placebo. In an 8-week study, the incidence of ALT or AST elevations ≥ 3 times the upper limit of normal was 13% in patients receiving dosages equivalent to 134 mg to 200 mg fenofibrate daily and was 0% in those receiving dosages equivalent to 34 mg to 67 mg fenofibrate daily or placebo.

Post-Marketing Experience

The following adverse reactions have been identified during post-approval use of fenofibrate: myalgia, rhabdomyolysis, pancreatitis, acute renal failure, muscle spasm, hepatitis, cirrhosis, increased total bilirubin, anemia, arthralgia, decreases in hemoglobin, decreases in hematocrit, white blood cell decreases, asthenia and interstitial lung disease. Because these reactions are reported voluntarily from a population of uncertain size, it is not always possible to reliably estimate their frequency or establish a causal relationship to drug exposure.

To report SUSPECTED ADVERSE REACTIONS, contact Glenmark Pharmaceuticals, Inc., USA at 1 (888) 721-7115 or FDA at 1-800-FDA-1088 or www.fda.gov/medwatch.

OVERDOSAGE

There is no specific treatment for overdose with fenofibrate. General supportive care of the patient is indicated, including monitoring of vital signs and observation of clinical status, should an overdose occur. If indicated, elimination of unabsorbed drug should be achieved by emesis or gastric lavage; usual precautions should be observed to maintain the airway. Because fenofibrate is highly bound to plasma proteins, hemodialysis should not be considered.

DOSAGE AND ADMINISTRATION

Patients should be placed on an appropriate lipid-lowering diet before receiving fenofibrate capsules, and should continue this diet during treatment with fenofibrate capsules. Fenofibrate capsules should be given with meals, thereby optimizing the bioavailability of the medication.

For the treatment of adult patients with primary hypercholesterolemia or mixed hyperlipidemia, the initial dose of fenofibrate capsules is 200 mg per day.

For adult patients with hypertriglyceridemia, the initial dose is 67 to 200 mg per day.

Dosage should be individualized according to patient response, and should be adjusted if necessary following repeat lipid determinations at 4 to 8 week intervals. The maximum dose is 200 mg per day.

Treatment with fenofibrate capsules should be initiated at a dose of 67 mg/day in patients having impaired renal function, and increased only after evaluation of the effects on renal function and lipid levels at this dose. In the elderly, the initial dose should likewise be limited to 67 mg/day.

Lipid levels should be monitored periodically and consideration should be given to reducing the dosage of fenofibrate capsules if lipid levels fall significantly below the targeted range.

HOW SUPPLIED

Fenofibrate Capsules, USP (micronized) 67 mg are size ‘4’ hard gelatin capsules with an opaque pink cap and body, imprinted in black ink with a Glenmark logo “G” and “580” on opposing cap and body portions of the capsule, filled with white to off-white granular powder. They are supplied as follows:

NDC 68462-580-01 Bottles of 100 capsules

Fenofibrate Capsules, USP (micronized) 134 mg are size ‘2’ hard gelatin capsules with an opaque light blue cap and body, imprinted in black ink with a Glenmark logo “G” and “581” on opposing cap and body portions of the capsule, filled with white to off-white granular powder. They are supplied as follows:

NDC 68462-581-01 Bottles of 100 capsules

Fenofibrate Capsules, USP (micronized) 200 mg are size ‘1’ hard gelatin capsules with an opaque orange cap and body, imprinted in black ink with a Glenmark logo “G” and “582” on opposing cap and body portions of the capsule, filled with white to off-white granular powder. They are supplied as follows:

NDC 68462-582-01 Bottles of 100 capsules

Storage

Store at 20°C to 25°C (68°F to 77°F) [see USP Controlled Room Temperature]. Keep out of the reach of children. Protect from moisture. Dispense in a tight, light-resistant container as defined in USP with a child-resistant closure (as required).

REFERENCES

1. GOLDBERG AC, et al. Fenofibrate for the Treatment of Type IV and V Hyperlipoproteinemias: A Double-Blind, Placebo-Controlled Multicenter US Study. Clinical Therapeutics, 11, pp. 69-83, 1989.
2. NIKKILA EA, Familial Lipoprotein Lipase Deficiency and Related Disorders of Chylomicron Metabolism. In Stanbury J.B., et al. (eds.): The Metabolic Basis of Inherited Disease, 5th edition, McGraw-Hill, 1983, Chap. 30, pp. 622-642.
3. BROWN WV, et al. Effects of Fenofibrate on Plasma Lipids: Double-Blind, Multicenter Study in Patients with Type IIA or IIB Hyperlipidemia. Arteriosclerosis. 6, pp. 670-678, 1986.

Distributed by:

Glenmark Pharmaceuticals Inc., USA

Elmwood Park, NJ 07407

Questions? 1 (888) 721-7115

www.glenmarkpharma-us.com

August 2025

Label Display Panel

NDC 68462-580-01

Fenofibrate Capsules, USP

67 mg

100’s count

Bottle Label

Label Display Panel

NDC 68462-581-01

Fenofibrate Capsules, USP

134 mg

100’s count

Bottle Label

Label Display Panel

NDC 68462-582-01

Fenofibrate Capsules, USP

200 mg

100’s count

Bottle Label